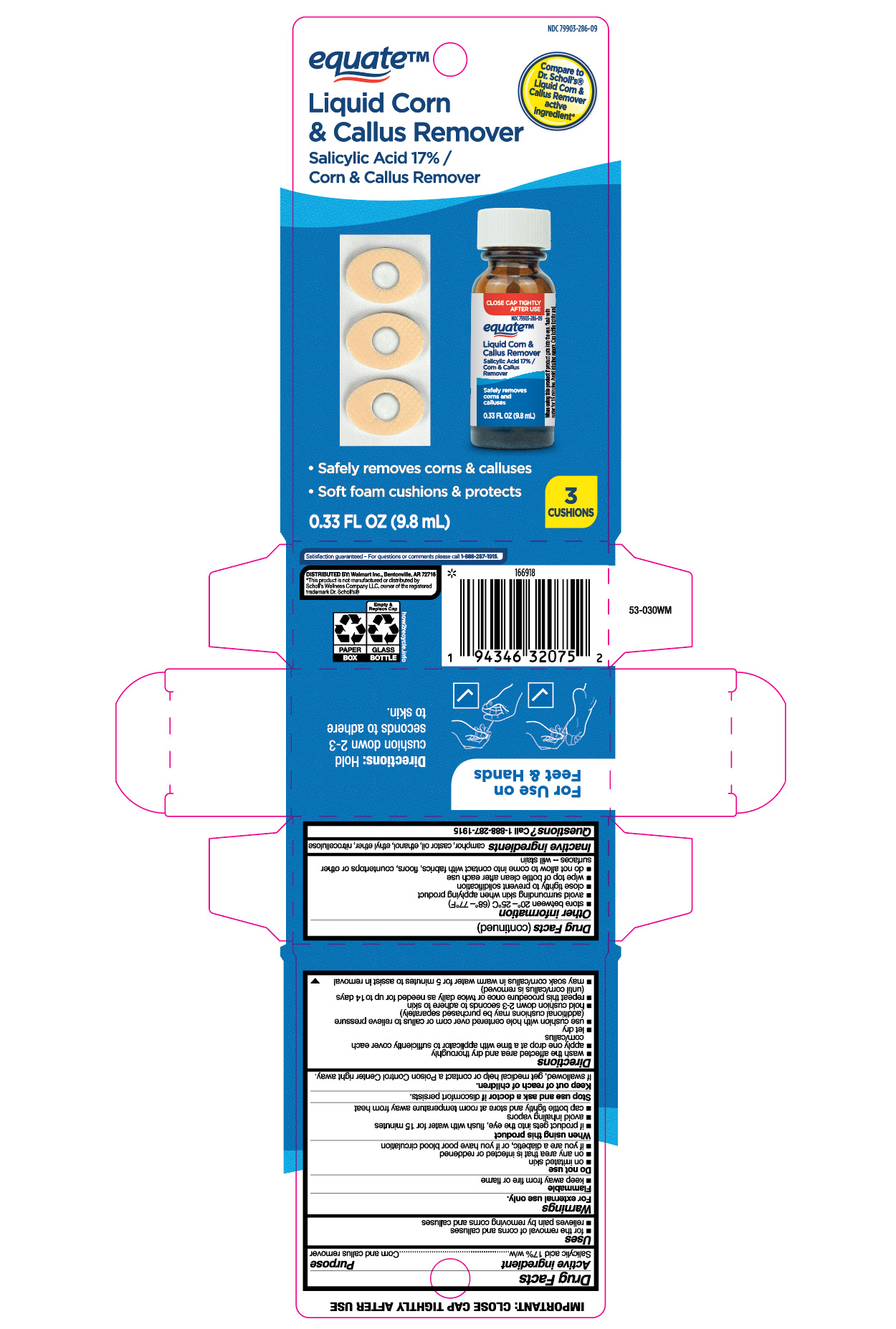 DRUG LABEL: Salicylic Acid
NDC: 79903-286 | Form: LIQUID
Manufacturer: Wal-Mart Stores, Inc.
Category: otc | Type: HUMAN OTC DRUG LABEL
Date: 20260205

ACTIVE INGREDIENTS: SALICYLIC ACID 170 mg/1 mL
INACTIVE INGREDIENTS: ALCOHOL; ETHYL ETHER; NITROCELLULOSE; CAMPHOR (NATURAL); CASTOR OIL

Equate Liquid Corn & Callus Remover

Active ingredient

Salicylic acid 17%w/w

Purpose

Corn and callus remover

Uses

- for the removal of corns and calluses
- relieves pain by removing corns and calluses

Warnings

For external use only.

Flammable

- keep away from fire or flame

Do not use

- on irritated skin
- on any area that is infected or reddened
- if you are a diabetic, or if you have poor blood circulation

When using this product

- if product gets into the eyes, flush with water for 15 minutes
- avoid inhaling vapors
- cap bottle tightly and store at room temperature away from heat

Stop and ask a doctor if

discomfort persists.

Keep out of reach of children.

If swallowed, get medical help or contact a Poison Control Center right away.

Directions

- wash the affected area and dry thoroughly
- apply one drop at a time with applicator to sufficiently cover each corn/callus
- let dry
- use cushion with hole centered over corn or callus to relieve pressure (additional cushions may be purchased separately)
- hold cushion down 2-3 seconds to adhere to skin
- repeat this procedure once or twice daily as needed for up to 14 days (until corn/callus is removed)
- may soak corn/callus in warm water for 5 minutes to assist in removal

Other information

- store between 20°C - 25°C (68°F - 77°F)
- avoid surrounding skin when applying product
- close tightly to prevent solidification
- wipe top of bottle clean after each use
- do not allow to come into contact with fabrics, floors, countertops or other surfaces--will stain

Inactive ingredients

camphor, castor oil, ethanol, ethyl ether, nitrocellulose

Questions?

Call 1-888-287-1915

Principal Display Panel

equate

Liquid Corn

& Callus Remover

Salicylic Acid 17% /

Corn & Callus Remover

- Safely removes corn & calluses
- Soft foam cushions & protects

3

Cushions

0.33 FL OZ (9.8 mL)